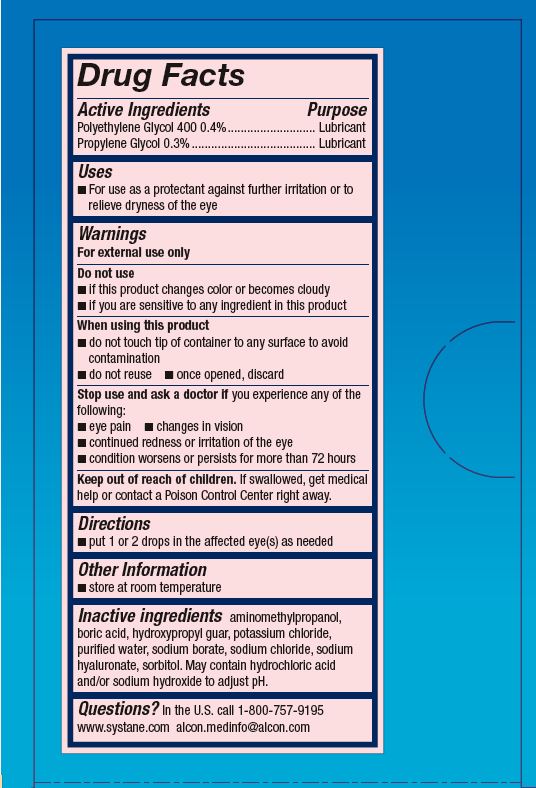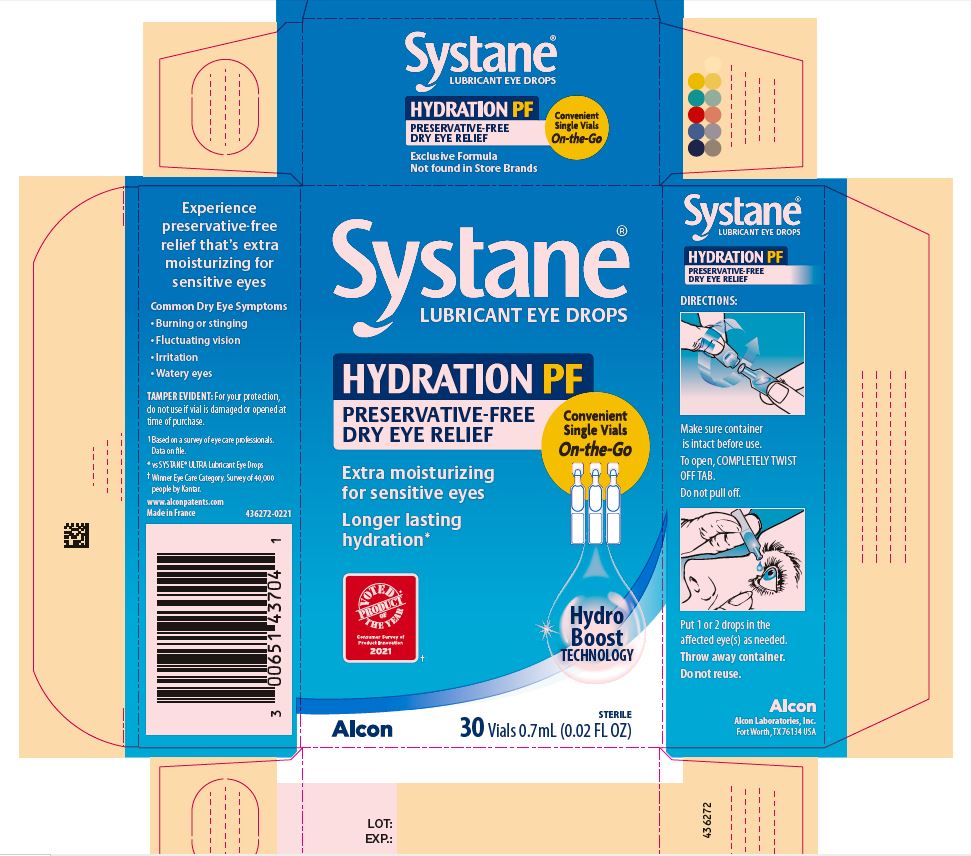 DRUG LABEL: SYSTANE HYDRATION PF PRESERVATIVE FREE
NDC: 0065-1437 | Form: SOLUTION/ DROPS
Manufacturer: Alcon Laboratories, Inc.
Category: otc | Type: HUMAN OTC DRUG LABEL
Date: 20231215

ACTIVE INGREDIENTS: Polyethylene Glycol 400 4 mg/1 mL; Propylene Glycol 3 mg/1 mL
INACTIVE INGREDIENTS: Aminomethylpropanol; Boric Acid; Guaraprolose (3500 Mpa.S At 1%); Potassium Chloride; Water; Sodium Borate; Sodium Chloride; Hyaluronate Sodium; Hydrochloric Acid; Sodium Hydroxide; Sorbitol

Drug Facts

ACTIVE INGREDIENT

Active Ingredients | Purpose
Polyethylene Glycol 400 0.4% | Lubricant
Propylene Glycol 0.3% | Lubricant

Uses

- for use as a protectant against further irritation or to relieve dryness of the eye

Warnings

For external use only

Do not use

- if this product changes color or becomes cloudy
- if you are sensitive to any ingredient in this product

When using this product

- do not touch tip of container to any surface to avoid contamination
- do not reuse
- once opened, discard

Stop use and ask a doctor if you experience any of the following:

- eye pain
- changes in vision
- continued redness or irritation of the eye
- condition worsens or persists for more than 72 hours

Keep out of reach of children.

If swallowed, get medical help or contact a Poison Control Center right away.

Directions

- put 1 or 2 drops in the affected eye(s) as needed.

Other information

- store at room temperature

Inactive ingredients

aminomethylpropanol, boric acid, hydroxypropyl guar, potassium chloride, purified water, sodium borate, sodium chloride, sodium hyaluronate, sorbitol. May contain hydrochloric acid and/or sodium hydroxide to adjust pH.

Questions?

In the U.S. call 1-800-757-9195
www.systane.com
alcon.medinfo@alcon.com

PRINCIPAL DISPLAY PANEL

SYSTANE®
Lubricant Eye Drops
HYDRATION PF
PRESERVATIVE-FREE
DRY EYE RELIEF
Convenient
Single Vials
On-the-Go
Extra moisturizing for sensitive eyes
Longer lasting hydration*
VOTED PRODUCT OF THE YEAR
Consumer Survey of Product Innovation
2021±
Hydro
Boost
TECHNOLOGY
Alcon
STERILE
30 Vials 0.7 mL (0.02 FL OZ)
Experience
preservative-free
relief that’s extra
moisturizing for
sensitive eyes
Common Dry Eye Symptoms
• Burning or stinging
• Fluctuating vision
• Irritation
• Watery eyes
TAMPER EVIDENT:
For your protection, do not use if vial is damaged or opened at time of purchase.
^1 Based on a survey of eye care professionals.
Data on file.
* vs SYSTANE® ULTRA Lubricant Eye Drops
±Winner Eye Care Category. Survey of 40,000
people by Kantar.
www.alconpatents.com
Made in France
436272-0221
SYSTANE® Lubricant Eye Drops
HYDRATION PF
PRESERVATIVE-FREE
DRY EYE RELIEF
DIRECTIONS:
Make sure container is intact before use.
To open, COMPLETELY TWIST OFF TAB.
Do not pull off.
Put 1 or 2 drops in the affected eye(s) as needed.
Throw away container.
Do not reuse.
ALCON
Alcon Laboratories, Inc.
Fort Worth, TX 76134 USA
LOT:
EXP.: